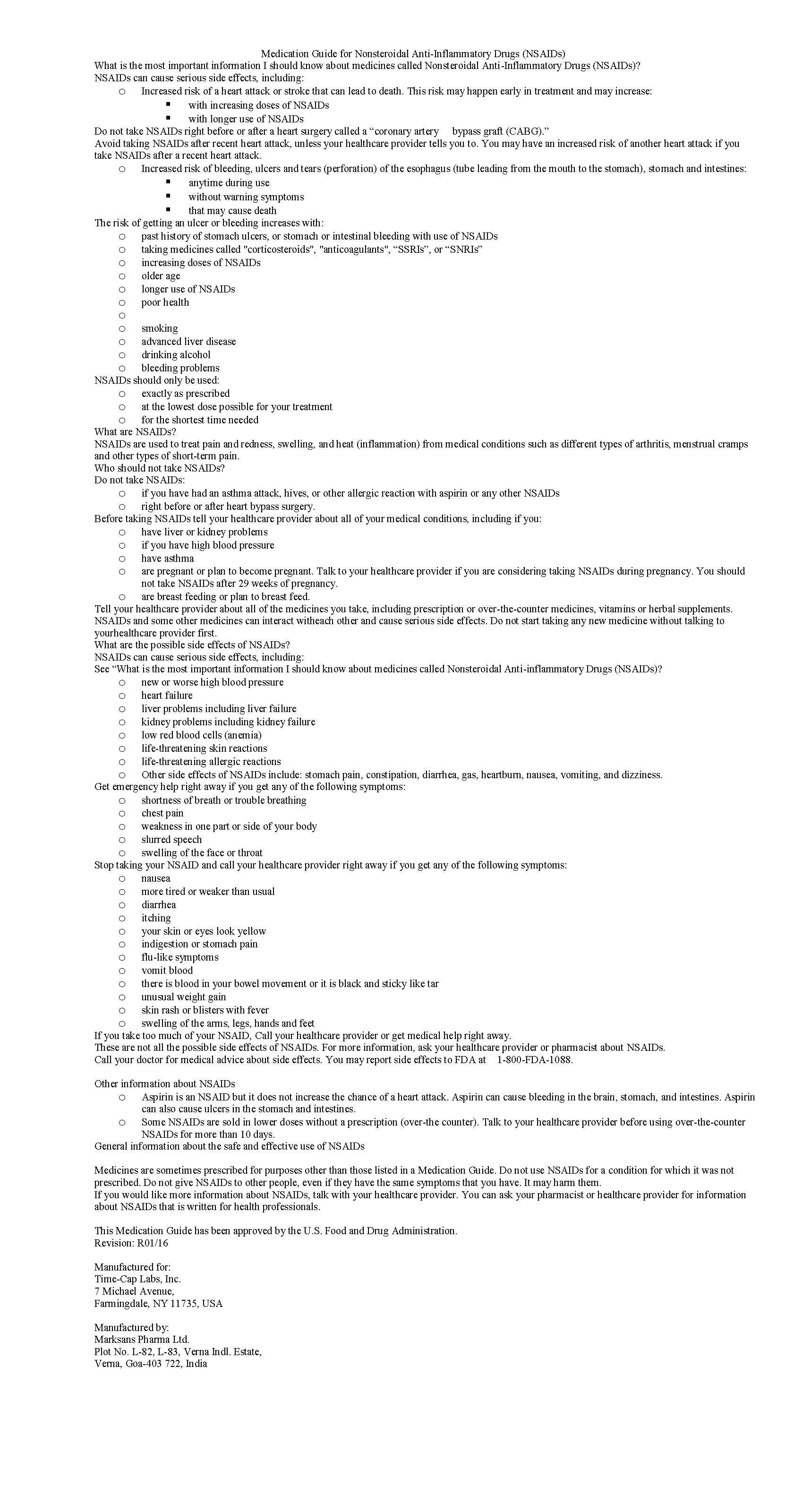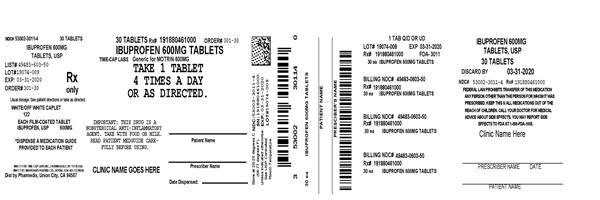 DRUG LABEL: IBUPROFEN
NDC: 53002-3011 | Form: TABLET, FILM COATED
Manufacturer: RPK Pharmaceuticals, Inc.
Category: prescription | Type: HUMAN PRESCRIPTION DRUG LABEL
Date: 20230607

ACTIVE INGREDIENTS: IBUPROFEN 600 mg/1 1
INACTIVE INGREDIENTS: SILICON DIOXIDE; CROSCARMELLOSE SODIUM; MAGNESIUM STEARATE; MICROCRYSTALLINE CELLULOSE; POLYETHYLENE GLYCOL, UNSPECIFIED; POLYVINYL ALCOHOL, UNSPECIFIED; STARCH, CORN; TALC; TITANIUM DIOXIDE

IBUPROFEN 400 MG - 600 MG AND 800 MG TABLETS

HOW SUPPLIED

Product: 53002-3011

NDC: 53002-3011-1 10 TABLET, FILM COATED in a BOTTLE

NDC: 53002-3011-2 15 TABLET, FILM COATED in a BOTTLE

NDC: 53002-3011-4 30 TABLET, FILM COATED in a BOTTLE

NDC: 53002-3011-5 50 TABLET, FILM COATED in a BOTTLE